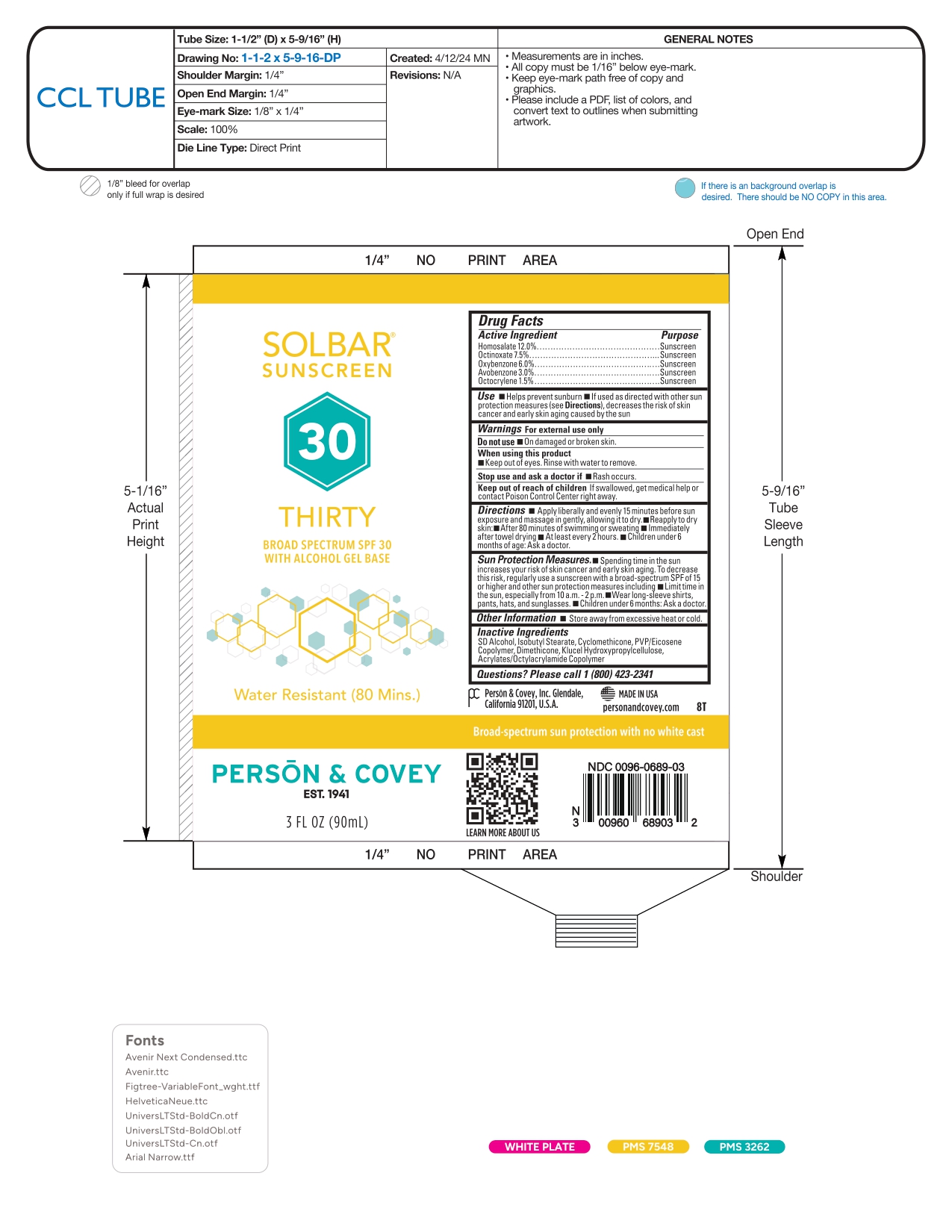 DRUG LABEL: SOLBAR THIRTY
NDC: 0096-0689 | Form: GEL
Manufacturer: Person and Covey
Category: otc | Type: HUMAN OTC DRUG LABEL
Date: 20260122

ACTIVE INGREDIENTS: OXYBENZONE 60 mg/1 g; OCTOCRYLENE 15 mg/1 g; AVOBENZONE 30 mg/1 g; OCTINOXATE 75 mg/1 g; HOMOSALATE 120 mg/1 g
INACTIVE INGREDIENTS: HYDROXYPROPYLCELLULOSE; ACRYLATES/OCTYLACRYLAMIDE COPOLYMER (75000 MW); ALCOHOL; ISOBUTYL STEARATE; DIMETHICONE; EICOSYL POVIDONE; CYCLOMETHICONE

SOLBAR THIRTY - sunscreen gel

Active Ingredient

Homosalate 12.0%

Octinoxate 7.5%

Oxybenzone 6.0%

Avobenzone 3.0%

Octocrylene 1.5%

Purpose

Sunscreen

Uses

Helps prevent sunburn. If used as directed with other sun protection measures (see Directions), decreases the risk of skin cancer and early skin aging caused by the sun.

Warnings

For external use only

Do not use on damaged or broken skin.

When using this product keep out of eyes. Rinse with water to remove.

Stop use and ask a doctor if rash occurs.

Keep out of reach of children.

If swallowed, get medical help or contact a Poison Control Center right away.

Directions

- Apply liberally 15 minutes before sun exposure.
- Reapply: after 80 minutes of swimming or sweating; immediately after towel drying; at least every 2 hours.

Sun Protection Measures:

- Spending time in the sun increases your risk of skin cancer and early skin aging.
- To decrease this risk, regularly use a sunscreen with a broad-spectrum SPF of 15 or higher and other sun protection measures including: limit time in the sun, especially from 10 a.m.-2 p.m.; wear long-sleeve shirts, pants, hats, and sunglasses.
- Children under 6 months: Ask a doctor.

Inactive Ingredients

SD Alcohol, Isobutyl Stearate, Cyclomethicone, PVP/Eicosene Copolymer, Dimethicone, Hydroxypropylcellulose, Acrylates/Octylacrylamide Copolymer.

Other Information

Store away from excessive heat or cold.

Questions?

Please call 1 (800) 423-2341

Company Information

Person & Covey, Inc. Glendale, California 91201, U.S.A. MADE IN USA personandcovey.com